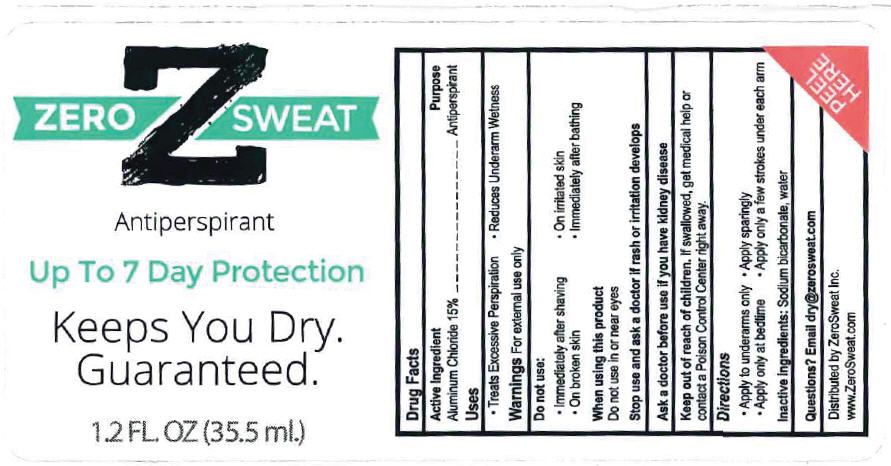 DRUG LABEL: ZeroSweat
NDC: 55726-048 | Form: LIQUID
Manufacturer: ZeroSweat Inc
Category: otc | Type: HUMAN OTC DRUG LABEL
Date: 20201015

ACTIVE INGREDIENTS: ALUMINUM CHLORIDE 15 mg/1 mL
INACTIVE INGREDIENTS: water; SODIUM BICARBONATE

Active Ingredients: Aluminum Chloride 15%

Purpose: Antiperspirant

Uses

- Treats Excessive Perspiration
- Reduces underarm wetness

Warnings:

For external use only.

Do not use:

- Immediately after shaving
- On broken skin
- On irritated skin
- Immediately after bathing

When using this product

- Do not use in or near eyes
- Apply to underarms only.

Stop use and ask a doctor if rash or irritation develops.

Ask a doctor before use if you have kidney disease.

Keep out of reach of children.

If swallowed, get medical help or contact a poison control center right away.

Directions

- Apply to underarms only.
- Apply only at bedtime.
- Apply sparingly.
- Apply only a few strokes under each arm,

Inactive Ingredients: Sodium bicarbonate,water

Questions?Email dry@zerosweat.com

PRINCIPAL DISPLAY PANEL - 35.5 ml Bottle Carton

Z
ZERO SWEAT

Antiperspirant

Up To 7 Day Protection

Keeps You Dry.
Guaranteed.

1.2 FL. OZ (35.5 ml.)